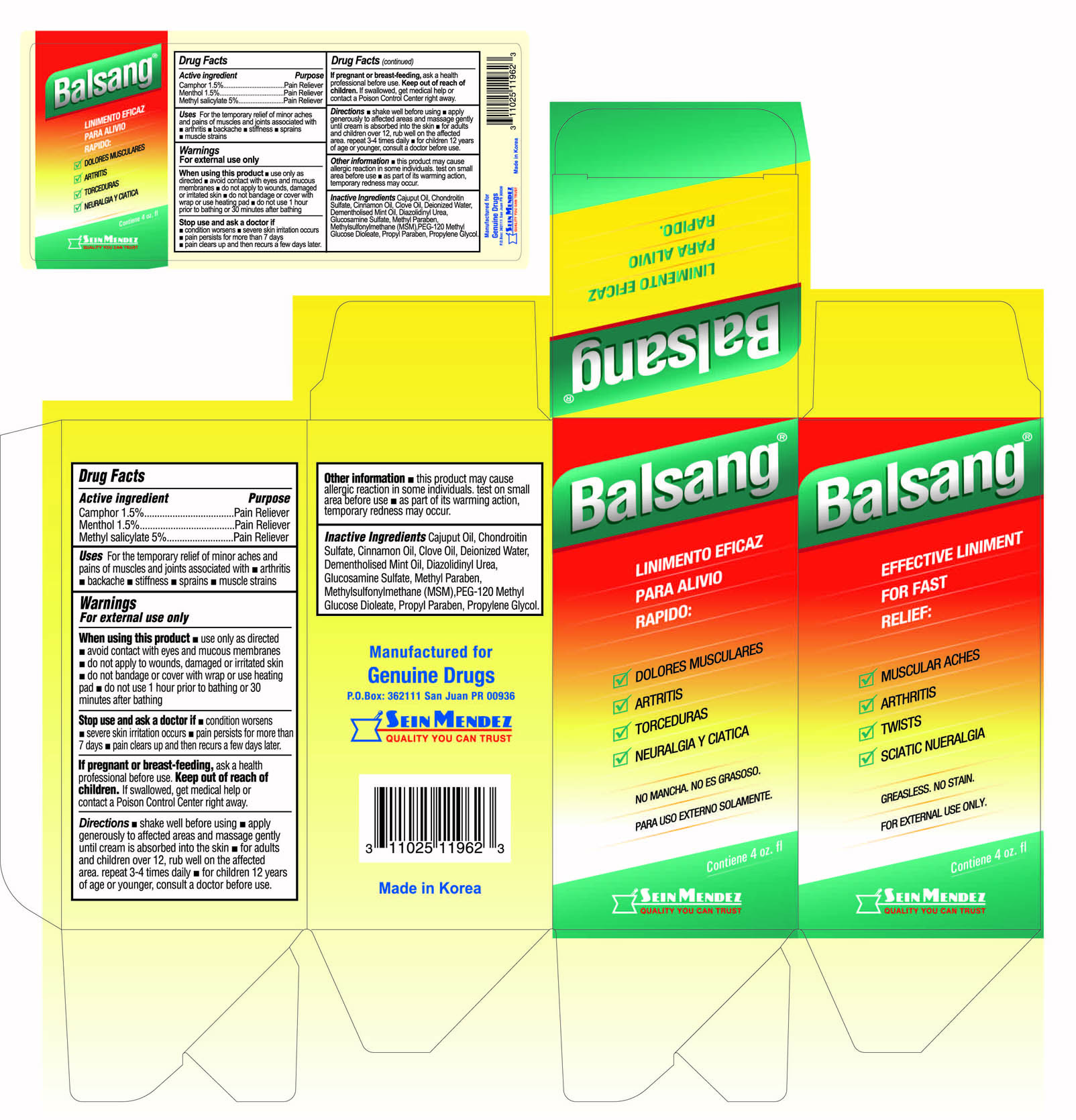 DRUG LABEL: Balsang Pain Relief
NDC: 69666-962 | Form: SOLUTION
Manufacturer: Genuine Drugs
Category: otc | Type: HUMAN OTC DRUG LABEL
Date: 20230217

ACTIVE INGREDIENTS: MENTHOL, (+)- 1.5 mg/100 mL; METHYL SALICYLATE 5 mg/100 mL; CAMPHOR, (-)- 1.5 mg/100 mL
INACTIVE INGREDIENTS: WATER; CAJUPUT OIL; CHONDROITIN SULFATE (BOVINE); CINNAMON OIL; CLOVE OIL; PEPPERMINT OIL; GLUCOSAMINE SULFATE; METHYLPARABEN; PEG-120 METHYL GLUCOSE DIOLEATE; PROPYLPARABEN; DIAZOLIDINYL UREA

Balsang Pain Relief

Active Ingredients

Camphor 1.5%

Menthol 1.5%

Methyl salicylate 5%

Uses

For the temporarily relieves minor aches and pains of muscle and joints associated with

- arthritis
- backache
- stiffness
- sprains
- muscle strains

WARNINGS

For external use only.

When using this product

- use only as directed
- avoid contact with eyes and mucous membranes
- do not apply to wounds, damaged or irritated skin
- do not bandage or cover with wrap or use heating pad
- do not use 1 hour prior to bathing or 30 minutes after bathing

Stop use and ask a doctor if

- condition worsens
- severe skin irritation occurs
- pain persists for more than 7 days
- pain clears up and then reocurs a few days later.

Keep out of reach of children

If swallowed, get medical help or contact a Poison Control Center immediately

If pregnant or breast-feeding

ask a health professional before use

Directions

- shake well before using
- apply generously to affected areas and massage gently until cream is absorbed into the skin
- for adults and children over 12, rub well on the affected area. repeat 3-4 times daily
- for children 12 years of age or younger, consult a doctor before use

Other information

- this product may cause allergic reactions in some individuals. test on small area before use
- as part of its warming action, temporary redness may occur.

Inactive Ingredients

Cajuput Oil, Chondroitin Sulfate, Cinnamon Oil, Clove Oil, Deionized Water, Dementholised Mint Oil, Deazolidinyl Urea, Glucosamine Sulfate, Methyl Paraben, Methylsulfonylmethane (MSM), PEG-12 Methyl Glucose Dioleate, Propyl Paraben, Propylene Glycol

PURPOSE

Pain Reliever

Pain Reliever

Pain Reliever

PACKAGE LABEL

Balsang Pain Relief